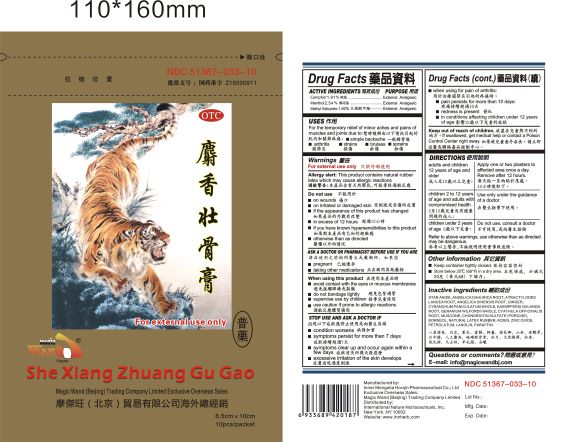 DRUG LABEL: SheXiang ZhuangGu Gao
NDC: 51367-033 | Form: PLASTER
Manufacturer: International Nature Nutraceuticals
Category: otc | Type: HUMAN OTC DRUG LABEL
Date: 20190402

ACTIVE INGREDIENTS: CAMPHOR (NATURAL) 30.53 mg/1 1; MENTHOL 40.71 mg/1 1; METHYL SALICYLATE 25.95 mg/1 1
INACTIVE INGREDIENTS: STAR ANISE; ANGELICA DAHURICA ROOT; ATRACTYLODES LANCEA ROOT; ANGELICA SINENSIS ROOT; GINGER; CYNANCHUM PANICULATUM WHOLE; KAEMPFERIA GALANGA ROOT; GERANIUM WILFORDII WHOLE; CYATHULA OFFICINALIS ROOT; MUSCONE; CHONDROITIN SULFATE (PORCINE); BORNEOL; NATURAL LATEX RUBBER; ROSIN; ZINC OXIDE; PETROLATUM; LANOLIN; PARAFFIN

Drug Facts

Active Ingredients

Camphor 1.91% External Analgesic

Menthol 2.54%: External Analgesic

Methyl Salicylate 1.62%: External Analgesic

Uses

For the temporary relief of minor aches and pains of muscles and joints due to:

Simple backache
Arthritis
Strains
Bruises
Sprains

Do Not Use

On wounds
On irritated or damaged skin
If the appearance of this product has changed
In excess of 12 hours
If known sensitivity this product
Otherwise than as Directed

Ask a doctor or pharmacist before use if you are:

Pregnant, or taking other medications

Stop Use and ask a doctor if

Condition worsens
Symptoms persist for more than 7 days
Symptoms clear up and occur again within a few days
Excessive irritation of the skin develops

When Using for pain of arthritis

Pain persists for more than 10 days
redness is present
In conditions affecting children under 12 years of age

Keep Out of Reach of Children

If swallowed get medical help or contact a Poision Control Center right away

Warnings:

For External Use Only

Directions

Adults and Children 12 years of age and older: apply one or two plasters to affected area once a day, remove after 12 hours

Children 2 to 12 years of age and adults with compromised health: use only the guidance of a doctor

Children under 2 years of age: do not use

Allergy Alert:

This product contains natural rubber latex which may cause allergic reactions

Other Information:

Keep container tightly closed

Store below 20C in a dry area.

Inactive Ingredients

STAR ANISE
ANGELICA DAHURICA ROOT
ATRACTYLODES LANCEA ROOT
ANGELICA SINENSIS ROOT
GINGER
CYNANCHUM PANICULATUM WHOLE
KAEMPFERIA GALANGA ROOT
GERANIUM WILFORDII WHOLE
CYATHULA OFFICINALIS ROOT
MUSCONE
CHONDROITIN SULFATE (PORCINE)
BORNEOL
NATURAL LATEX RUBBER
ROSIN
ZINC OXIDE
PETROLATUM
LANOLIN
PARAFFIN